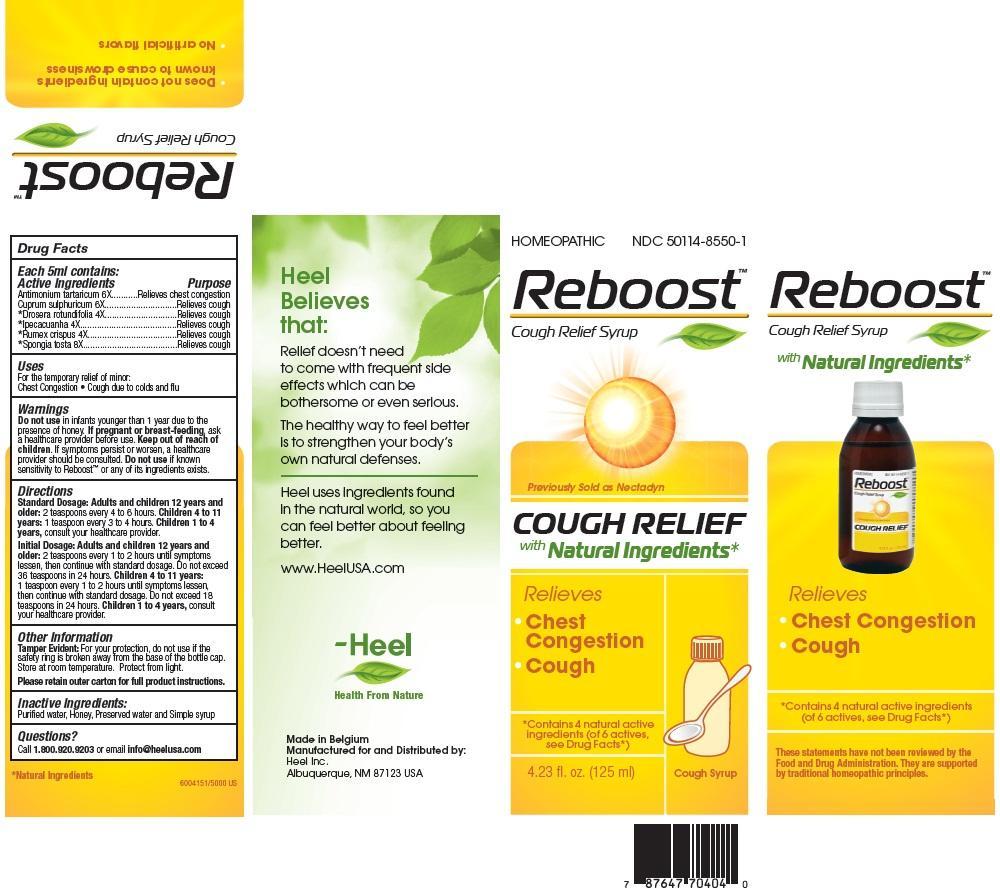 DRUG LABEL: Reboost
NDC: 50114-8550 | Form: SYRUP
Manufacturer: Heel Inc
Category: homeopathic | Type: HUMAN OTC DRUG LABEL
Date: 20130213

ACTIVE INGREDIENTS: ANTIMONY POTASSIUM TARTRATE 6 [hp_X]/125 mL; CUPRIC SULFATE 6 [hp_X]/125 mL; DROSERA ROTUNDIFOLIA 4 [hp_X]/125 mL; IPECAC 4 [hp_X]/125 mL; RUMEX CRISPUS ROOT 4 [hp_X]/125 mL; SPONGIA OFFICINALIS SKELETON, ROASTED 8 [hp_X]/125 mL
INACTIVE INGREDIENTS: WATER; HONEY; PROPYLENE GLYCOL; METHYLPARABEN; PROPYLPARABEN; SUCROSE

Reboost Cough Syrup

ACTIVE INGREDIENTS

Active Ingredients: Each 5ml contains: Antimonium tartaricum 6X, Cuprum sulphuricum 6X, Drosera rotundifolia 4X, Ipecacuanha 4X, Rumex crispus 4X, Spongia tosta 8X

INACTIVE INGREDIENTS

Inactive Ingredients: Purified Water, Honey, Preserved water and Simple syrup

PURPOSE

Antimonium tartaricum 6X..............Relieves chest congestion

Cuprum sulphuricum 6X.................Relieves cough

Drosera rotundifolia 4X..................Relieves cough

Ipecacuanha 4X.............................Relieves cough

Rumex crispus 4X...........................Relieves cough

Spongia tosta 8X...........................Relieves cough

DOSAGE AND ADMINISTRATION

Standard Dosage: Adults and children 12 years and older: 2 teaspoons every 4 to 6 hours.

Children 4 to 11 tears: 1 teaspoon every 3 to 4 hours.

Children 1 to 4 years, consult your healthcare provider.

Initial Dosage: Adults and children 12 years and older: 2 teaspoons every 1 to 2 hours until symptoms lessen, then continue with standard dosage. Do not exceed 36 teaspoons in 24 hours.

Children 4 to 11 tears: 1 teaspoon every 1 to 2 hours until symptoms lessen, then continue with standard dosage. Do not exceed 18 teaspoons in 24 hours.

Children 1 to 4 years, consult your healthcare provider.

WARNINGS

Do not use in infants younger than 1 year due to the presence of honey. If pregnant or breast-feeding, ask a healthcare provider before use. Keep out of reach of children. If symptoms persist or worsen, a healthcare provider should be consulted. Do not use if known sensitivity to Reboost or any of its ingredients exists.

KEEP OUT OF REACH OF CHILDREN

INDICATIONS AND USAGE

For the temporary relief of minor:

- Chest Congestion
- Cough due to colds and flu